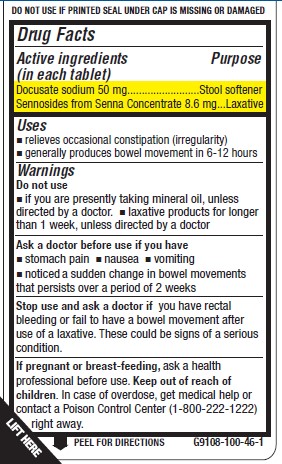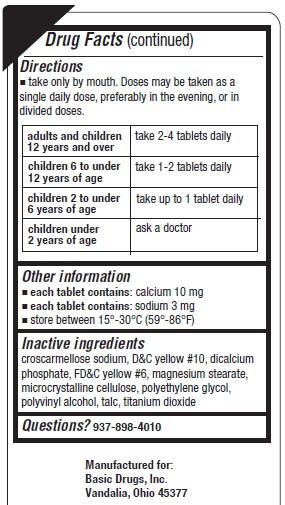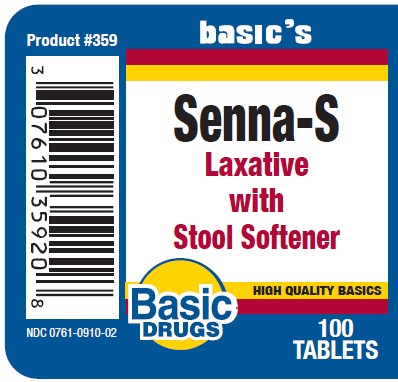 DRUG LABEL: SENNA-S

NDC: 0761-0910 | Form: TABLET
Manufacturer: Basic Drugs, Inc.
Category: otc | Type: HUMAN OTC DRUG LABEL
Date: 20240914

ACTIVE INGREDIENTS: DOCUSATE SODIUM 50 mg/1 1; SENNOSIDES 8.6 mg/1 1
INACTIVE INGREDIENTS: CROSCARMELLOSE SODIUM; D&C YELLOW NO. 10; ANHYDROUS DIBASIC CALCIUM PHOSPHATE; FD&C YELLOW NO. 6; MAGNESIUM STEARATE; CELLULOSE, MICROCRYSTALLINE; POLYETHYLENE GLYCOL, UNSPECIFIED; POLYVINYL ALCOHOL, UNSPECIFIED; TALC; TITANIUM DIOXIDE

BASIC DRUGS - SENNA-S - LAXATIVE WITH STOOL SOFTENER (0761-0910)

Active ingredient (in each tablet)

Docusate Sodium 50mg

Sennosides from Senna Concentrate 8.6mg

Purpose

Stool softener

Laxative

Uses

- relieves ocasional constipation (irregularity)
- generally produces bowel movement in 6-12 hours.

Warnings

Do not use

- if you are taking mineral oil, unless directed by a doctor.
- laxative products for longer than 1 week, unless directed by a doctor

Ask a doctor before use if you have

- stomach pain
- nausea
- vomiting
- noticed a sudden change in bowel movements that persists over a period of 2 weeks

Stop use and ask a doctor if you have rectal bleeding or you fail to have a bowel movement after use of a laxative. These could be signs of a serious condition.

If pregnant or breast-feeding, ask a health professional before use.

Keep out of reach of children. In case of overdose, get medical help or contact a Poison Control Center (1-800-222-1222) right away.

Directions

- take only by mouth. Doses may be taken as a single daily dose, preferably in the evening, or in divided doses.

adults and children 12 years of age and over | 2-4 tablets daily
children 6 to under 12 years | 1-2 tablets daily
children 2 to under 6 years | up to tablet daily
children under 2 years of age | ask a doctor

Other information

- each tablet contains: calcium 10 mg
- each tablet contains: sodium 3 mg
- store between 15° - 30°C (59° - 86°F)

Inactive ingredients

Croscarmellose sodium, D&C Yellow #10, dicalcium phosphate, FD&C Yellow # 6, magnesium stearate, microcrystalline cellulose, polyethylene glycol, polyvinyl alcohol, talc, titanium dioxide

Questions?

937-898-4010